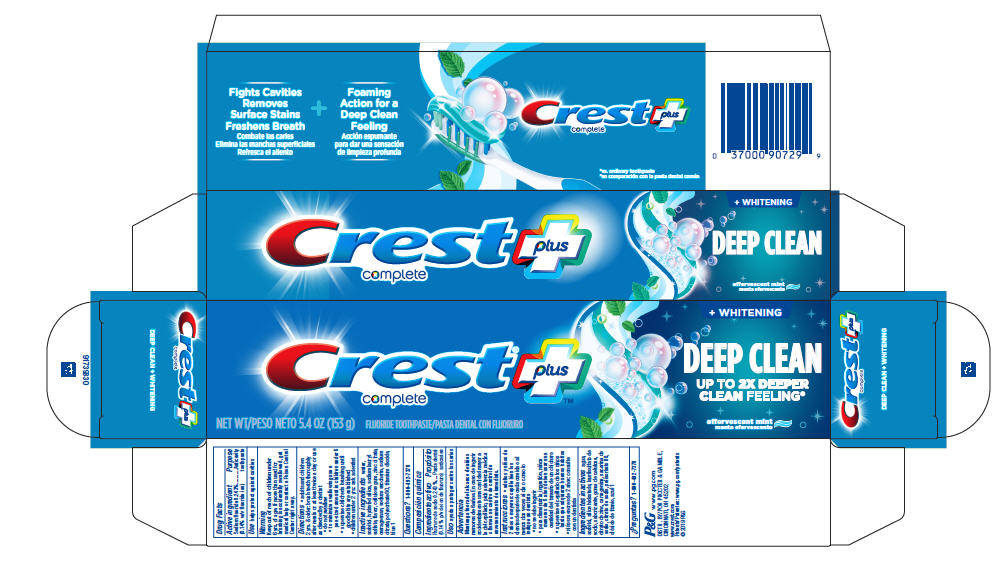 DRUG LABEL: Crest complete plus
NDC: 37000-946 | Form: PASTE, DENTIFRICE
Manufacturer: The Procter & Gamble Manufacturing Company
Category: otc | Type: HUMAN OTC DRUG LABEL
Date: 20260108

ACTIVE INGREDIENTS: SODIUM FLUORIDE 1.4 mg/1 g
INACTIVE INGREDIENTS: SORBITOL; WATER; HYDRATED SILICA; POLYSORBATE 80; SODIUM LAURYL SULFATE; ZINC CITRATE; CARBOXYMETHYLCELLULOSE SODIUM; CARRAGEENAN; SACCHARIN SODIUM; SODIUM CITRATE; TITANIUM DIOXIDE; FD&C BLUE NO. 1

Crest®
complete plus
Whitening Deep Clean

Drug Facts

Active ingredient

Sodium fluoride 0.243% (0.14% w/v fluoride ion)

Purpose

Anticavity toothpaste

Use

helps protect against cavities

Warnings

Keep out of reach of children under 6 yrs. of age. If more than used for brushing is accidentally swallowed, get medical help or contact a Poison Control Center right away.

Directions

- adults and children 2 yrs. & older: brush teeth thoroughly after meals or at least twice a day or use as directed by a dentist
- do not swallow
- to minimize swallowing use a pea-sized amount in children under 6
- supervise children's brushing until good habits are established
- children under 2 yrs.: ask a dentist

Inactive ingredients

water, sorbitol, hydrated silica, sodium lauryl sulfate, flavor, cellulose gum, zinc citrate, carrageenan, sodium saccharin, sodium citrate, polysorbate 80, titanium dioxide, blue 1

Questions?

1-800-492-7378

DISTR. BY PROCTER & GAMBLE,
CINCINNATI, OH 45202

PRINCIPAL DISPLAY PANEL - 153 g Tube Carton

Crest®plus
complete
NET WT 5.4 OZ (153 g)

FLUORIDE TOOTHPASTE

+ WHITENING

DEEP CLEAN

UP TO 2X DEEPER CLEAN FEELING*

effervescent mint